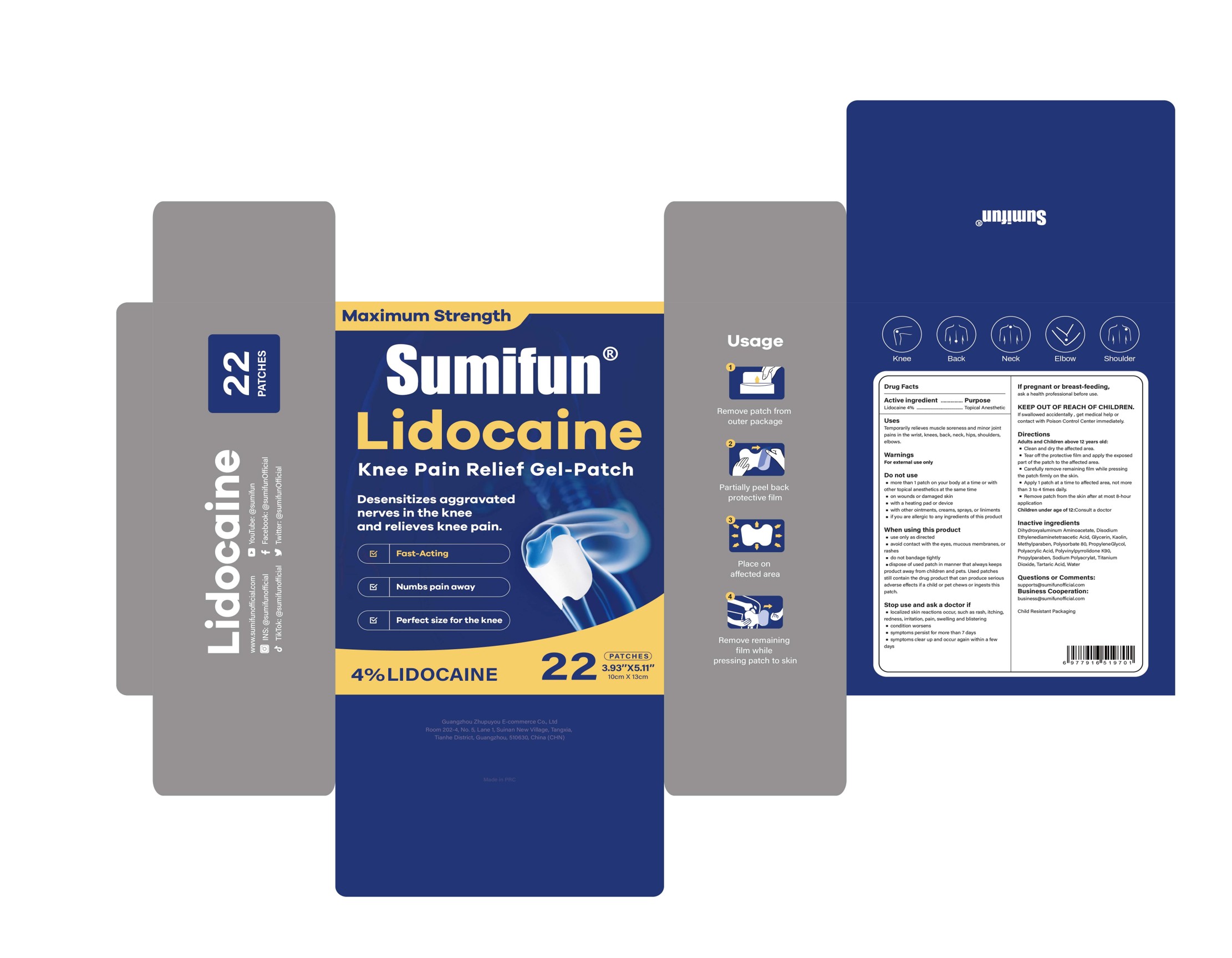 DRUG LABEL: Lidocaine Knee Pain Relief Gel-Patch
NDC: 84165-014 | Form: PATCH
Manufacturer: Guangzhou Zhupuyou E-commerce Co., Ltd
Category: otc | Type: HUMAN OTC DRUG LABEL
Date: 20250624

ACTIVE INGREDIENTS: LIDOCAINE 0.04 g/1 g
INACTIVE INGREDIENTS: METHYLPARABEN; POVIDONE K90; TARTARIC ACID; TITANIUM DIOXIDE; WATER; SODIUM POLYACRYLATE (2500000 MW); POLYSORBATE 80; DIHYDROXYALUMINUM AMINOACETATE ANHYDROUS; EDETATE DISODIUM; GLYCERIN; PROPYLENE GLYCOL; PROPYLPARABEN; KAOLIN; POLYACRYLIC ACID (250000 MW)

84165-014 Lidocaine Knee Pain Relief Gel-Patch

ACTIVE INGREDIENT

Lidocaine 4%

PURPOSE

Topical Anesthetic

INDICATIONS AND USAGE

Temporarily relieves muscie soreness and minor jointpains in the wrist, knecs, back, neck, hips, shoulders.elboxws.

WARNINGS

For external use only

DO NOT USE

more than 1 patch on your body at a time or with other topical anesthetics at the same time.
on wounds or damaged skin.
with a heating pad or device
with other ointments, creams, sprays, or liniments
if you are allergic to any ingredients of this product

WHEN USING

use only as directed
s avoid contact with the eyes, mucous membranes, orrashes
do not bandage tightly
dispose of used patch in manner that always keeps product away from children and pets. Used patche still contain the drug product that can produce serious adverse eflects if a child or pet chews or ingests this patch

STOP USE

localized skin reactions occur, such as rash, itchingredness, iritation, pain, swelng and blistering
condition worsens
symptoms persist for more than 7 days
symptoms clear up and occur again within a few days

KEEP OUT OF REACH OF CHILDREN

lf swallowved accidentally , get medical help orcontact with Poison Control Center immediately

DOSAGE AND ADMINISTRATION

Adults and Children above 12 years old:
Clean and dry the affected area.

Tear off the protective film and apply the exposed part of the patch to the affected area.

Carefully remwe remaining film while pressing the patch firmly on the skin.

Apply 1 patch at a time to afiected area, not morethan 3 to 4 times dally.

Remove patch from the skin after at most 8-hour application
Children under age of 12:Consuit a doctor

INACTIVE INGREDIENT

Dihydroxyaluminum Aminoacetate Anhydrous
Edetate Disodium
Glycerin
Kaolin
Methylparaben
Polyacrylic Acid
Polysorbate 80
PolyvinylPyrrolidone K90
Propylene Glycol
Propylparaben
Sodium Polyacrylate
Tartaric Acid
Titanium Dioxide
Water